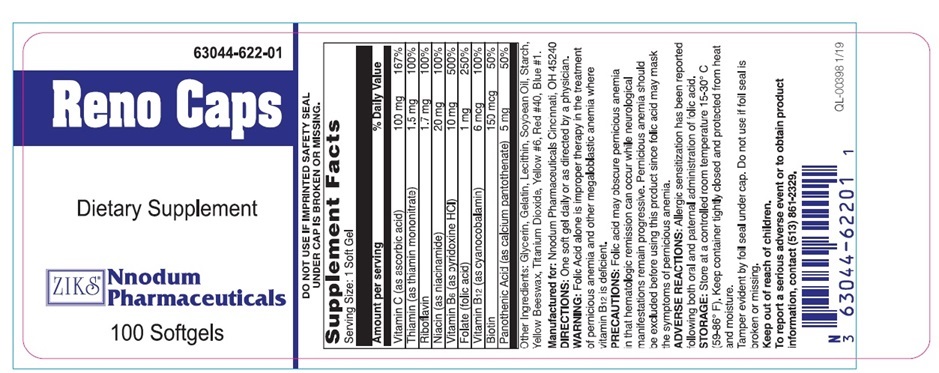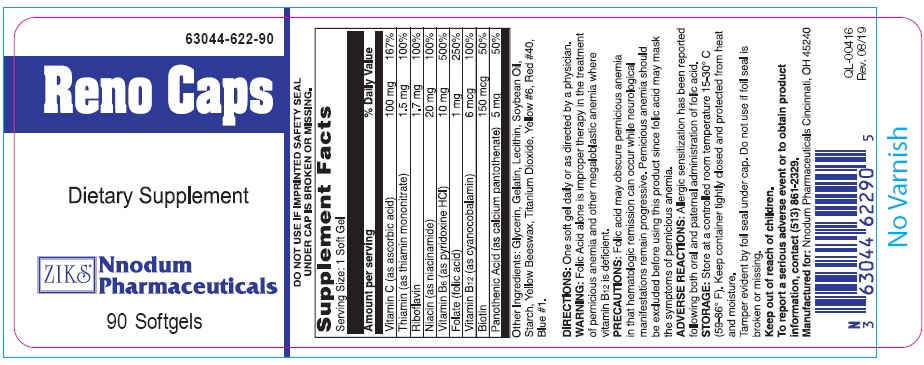 DRUG LABEL: RENO CAPS
                
NDC: 63044-622 | Form: CAPSULE
Manufacturer: Nnodum Pharmaceuticals
Category: other | Type: DIETARY SUPPLEMENT
Date: 20251229

ACTIVE INGREDIENTS: ASCORBIC ACID 100 mg/1 1; THIAMINE 1.5 mg/1 1; RIBOFLAVIN 1.7 mg/1 1; NIACIN 20 mg/1 1; PYRIDOXINE 10 mg/1 1; FOLIC ACID 1 mg/1 1; BIOTIN 150 ug/1 1; PANTOTHENIC ACID 5 mg/1 1; CYANOCOBALAMIN 6 ug/1 1
INACTIVE INGREDIENTS: GELATIN; GLYCERIN; LECITHIN, SOYBEAN; SOYBEAN OIL; TITANIUM DIOXIDE; FD&C YELLOW NO. 6; WATER; FD&C BLUE NO. 1; FD&C RED NO. 40

Reno Caps

DESCRIPTION

Reno Caps are black oval softgel imprinted “z622”. These softgels provide water- soluble vitamins.

Active Ingredients:

Each Reno Caps softgel contains:

Vitamin C (Ascorbic Acid)………………………100 mg

Thiamine (as thiamine mononitrate)……………..1.5 mg

Riboflavin………………………………………..1.7 mg

Niacin (as niacinamide)………………………….20 mg

Vitamin B-6 (as pyridoxine Hcl)………………...10 mg

Folate (as folic Acid)…………………………….1 mg

Vitamin B-12 (as cyanocobalam)………………..6 mcg

Biotin……………………………………………..150 mcg

Pantothenic acid (as calcium Pantothenate)……...5 mg

Inactive Ingredients: Gelatin, glycerin, lecithin, soybean oil, yellow beeswax, titanium dioxide, FDC Yellow #6, water, FDC blue #1, FDC Red #40

Health Claim

Reno Caps Softgels is a prescription vitamins supplement indicated for renal disease patients to replace critical vitamins lost due to dialysis in patients with chronic renal disease, uremia and impaired metabolic kidney functions. Also used as a stress vitamin.

Warnings

WARNING: Folic acid alone is improper therapy in the treatment of pernicious anemia and other megaloblastic anemia where vitamin B12 is deficient.

Directions

DIRECTIONS: One soft gel daily or as directed by a physician.

PRECAUTIONS

PRECAUTIONS: Folic acid may mask the symptoms of pernicious anemia in that hematologic remission may occur while neurological manifestations progressive. Pernicious anemia should be excluded before using this product since folic acid may mask the symptoms of pernicious anemia.

Safe handling

STORAGE: Store at controlled room temperature 15-30o C (59-86o F). Keep container tightly closed and protect from heat and moisture.

Package Label Principal Display Panel

Reno Caps 100-Count Bottle

62044-622-01

Reno Caps

Dietary Supplement

Nnodum
Pharmaceuticals

100 Softgels

Manufactured for: Nnodum Pharmaceuticals
Cincinnati, OH 45240

100 Softgels

90 Softgels

res